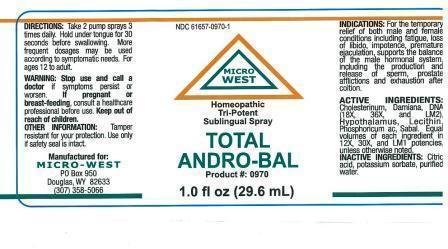 DRUG LABEL: TOTAL ANDRO-BAL
NDC: 61657-0970 | Form: LIQUID
Manufacturer: WHITE MANUFACTURING INC. DBA MICRO WEST
Category: homeopathic | Type: HUMAN OTC DRUG LABEL
Date: 20140812

ACTIVE INGREDIENTS: TURNERA DIFFUSA LEAFY TWIG 12 [hp_X]/30 mL; EGG PHOSPHOLIPIDS 12 [hp_X]/30 mL; PHOSPHORIC ACID 12 [hp_X]/30 mL; SAW PALMETTO 12 [hp_X]/30 mL; CHOLESTEROL 12 [hp_X]/30 mL; HERRING SPERM DNA 12 [hp_X]/30 mL; BOS TAURUS HYPOTHALAMUS 12 [hp_X]/30 mL; SUS SCROFA ADRENAL GLAND 12 [hp_X]/30 mL; PRASTERONE 12 [hp_X]/30 mL; PREGNENOLONE 12 [hp_X]/30 mL; PROGESTERONE 12 [hp_X]/30 mL; TESTOSTERONE 12 [hp_X]/30 mL
INACTIVE INGREDIENTS: POTASSIUM SORBATE; CITRIC ACID MONOHYDRATE

DRUG FACTS

ACTIVE INGREDIENTS

Cholesterium 18X,36X,LM2

Damiana 18X,36X,LM2

DNA 18X, 36X,LM2

Hypothalamus 12X,30X,LM1

Lechithinum 12X,30X,LM1

Phosphoricum acidum 12X,30X,LM1

Sabal 12X,30X,LM1

KEEP OUT OF REACH OF CHILDREN

PURPOSE

FOR BOTH MALE AND FEMALE conditions including fatigue, loss of libido, impotence, premature ejaculation supports the balance of the male hormonal system, including the production and release of sperm, prostate afflictions and exhaustion after coition

DIRECTIONS

DIRECTIONS: TAKE 2 PUMP SPRAYS 3 TIMES DAILY. HOLD UNDER TONGUE 30 SECONDS BEFORE SWALLOWING. MORE FREQUENT DOSAGES MAY BE USED ACCORDING TO SYMPTOMATIC NEEDS. FOR AGEWS 12 TO ADULT.

INDICATIONS

For the temporary relief of FOR BOTH MALE AND FEMALE conditions including fatigue, loss of libido, impotence, premature ejaculation supports the balance of the male hormonal system, including the production and release of sperm, prostate afflictions and exhaustion after coition

WARNING

WARNING: STOP USE AND CALL DOCROR if symptoms persist or worsen.

Other information: Tamper resistant for your protection. Use only if safety seal is intact

PREGNANCY OR BREAST-FEEDING

If pregnant or breast-feeding consult a healthcare professional before use

INACTIVE INGREDIENT

POTASSIUM SORBATE 0.1%

CITRIC ACID 0.0075%

Purified water

MANUFACTURE

MANUFACTURED FOR

MICRO-WEST

P.O. Box 950

DOUGLAS ,WY 82633

1-307-358-5066